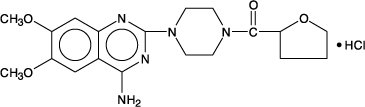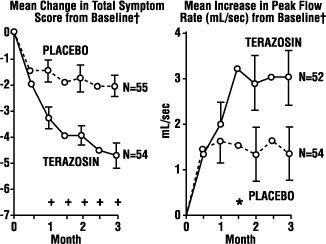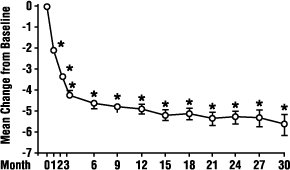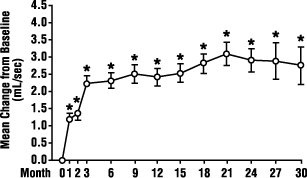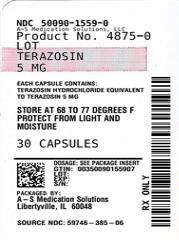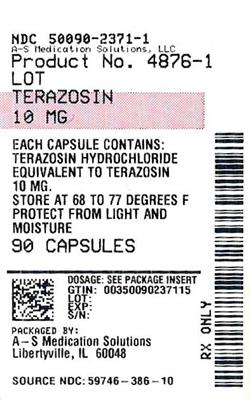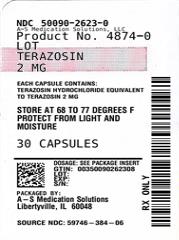 DRUG LABEL: Terazosin 
NDC: 50090-1559 | Form: CAPSULE
Manufacturer: A-S Medication Solutions
Category: prescription | Type: Human Prescription Drug Label
Date: 20260220

ACTIVE INGREDIENTS: TERAZOSIN HYDROCHLORIDE 5 mg/1 1
INACTIVE INGREDIENTS: GELATIN; Lactose Monohydrate; Magnesium Stearate; Sodium Lauryl Sulfate; TITANIUM DIOXIDE; STARCH, CORN; SILICA; KI203; AKA104(1); CURRY RED

TERAZOSIN CAPSULES, USP

DESCRIPTION

Terazosin hydrochloride, an alpha-1-selective adrenoceptor blocking agent, is a quinazoline derivative represented by the following chemical name,molecular formula and structural formula:
(RS)-Piperazine, 1-(4-amino-6,7-dimethoxy-2-quinazolinyl)-4-[(tetrahydro-2-furanyl)carbonyl]-, monohydrochloride.C19H26ClN5O4

Terazosin hydrochloride is a white, crystalline substance, freely soluble in water and isotonic saline and has a molecular weight of 423.93. Each capsule, for oral administration, contains 1 mg, 2 mg, 5 mg or 10 mg of terazosin as terazosin hydrochlolde. In addition, each capsule contains the following inactive ingredients: colloidal silicon dioxide, lactose monohydrate, magnesium stearate, and pregelatinized starch. The gelatin capsule contains gelatin, silicon dioxide, sodium lauryl sulfate, and titanium dioxide. The 1 mg shell also contains black iron oxide; the 2 mg capsule shell also contains D&C Yellow #10; the 5 mg capsule shell also contains D&C Yellow #10, FD&C Red #40 and D&C Red #28; the 10 mg capsule shell also contains FD&C Green #3 and D&C Yellow#10.

CLINICAL PHARMACOLOGY

Pharmacodynamics

A. Benign Prostatic Hyperplasia (BPH)

The symptoms associated with BPH are related to bladder outlet obstruction, which is comprised of two underlying components: a static component and a dynamic component. The static component is a consequence of an increase in prostate size. Over time, the prostate will continue to enlarge. However, clinical studies have demonstrated that the size of the prostate does not correlate with the severity of BPH symptoms or the degree of urinary obstruction. The dynamic component is a function of an increase in smooth muscle tone in the prostate and bladder neck, leading to constriction of the bladder outlet. Smooth muscle tone is mediated by sympathetic nervous stimulation of alpha-1 adrenoceptors, which are abundant in the prostate, prostatic capsule and bladder neck. The reduction in symptoms and improvement in urine flow rates following administration of terazosin is related to relaxation of smooth muscle produced by blockade of alpha-1 adrenoceptors in the bladder neck and prostate. Because there are relatively few alpha-1 adrenoceptors in the bladder body, terazosin is able to reduce the bladder outlet obstruction without affecting bladder contractility.

Terazosin has been studied in 1222 men with symptomatic BPH. In three placebo-controlled studies, symptom evaluation and uroflowmetric measurements were performed approximately 24 hours following dosing. Symptoms were quantified using the Boyarsky Index. The questionnaire evaluated both obstructive (hesitancy, intermittency, terminal dribbling, impairment of size and force of stream, sensation of incomplete bladder emptying) and irritative (nocturia, daytime frequency, urgency, dysuria) symptoms by rating each of the 9 symptoms from 0 to 3, for a total score of 27 points. Results from these studies indicated that terazosin statistically significantly improved symptoms and peak urine flow rates over placebo as follows:

 | Symptom Score |  | Change % | Peak Flow Rate |  | Change %
 | Range (0-27) |  | Change % | (mL/sec) |  | Change %
 | Mean | Mean | Change % | Mean | Mean | Change %
 | N | Baseline | Change % | N | Baseline | Change %
Study 1 (10 mg)a
Titration to fixed dose (12 wks)
Placebo | 55 | 9.7 | -2.3 (24) | 54 | 10.1 | +1.0 (10)
Terazosin | 54 | 10.1 | -4.5 (45)* | 52 | 8.8 | +3.0 (34)*
Study 2 (2, 5, 10, 20 mg)b
Titration to Response (24 wks)
Placebo | 89 | 12.5 | -3.8 (30) | 88 | 8.8 | +1.4 (16)
Terazosin | 85 | 12.2 | -5.3 (43)* | 84 | 8.4 | +2.9 (35)*
Study 3 (1, 2, 5, 10 mg)c
Titration to response (24 wks)
Placebo | 74 | 10.4 | -1.1 (11) | 74 | 8.8 | +1.2 (14)
Terazosin | 73 | 10.9 | -4.6 (42)* | 73 | 8.6 | +2.6 (30)*

a Highest dose 10 mg shown.
b 23% of patients on 10mg, 41% of patients on 20 mg.
c 67% of patients on 10 mg.
*Significantly (p ≤ 0.05) more improvement than placebo.

In all three studies, both symptom scores and peak urine flow rates showed statistically significant improvement from baseline in patients treated with terazosin capsules from week 2 (or the first clinic visit) and throughout the study duration.

Analysis of the effect of terazosin capsules on individual urinary symptoms demonstrated that compared to placebo, terazosin significantly improved the symptoms of hesitancy, intermittency, impairment in size and force of urinary stream, sensation of incomplete emptying, terminal dribbling, daytime frequency and nocturia.

Global assessments of overall urinary function and symptoms were also performed by investigators who were blinded to patient treatment assignment. In studies 1 and 3, patients treated with terazosin had a significantly (p ≤ 0.001) greater overall improvement compared to placebo treated patients.

In a short term study (Study 1), patients were randomized to either 2, 5 or 10 mg of terazosin or placebo. Patients randomized to the 10 mg group achieved a statistically significant response in both symptoms and peak flow rate compared to placebo (Figure 1).

FIGURE 1., STUDY 1

† for baseline values see above table

* p ≤ 0.05, compared to placebo group

In a long-term, open-label, non-placebo controlled clinical trial, 181 men were followed for 2 years and 58 of these men were followed for 30 months. The effect of terazosin on urinary symptom scores and peak flow rates was maintained throughout the study duration (Figures 2 and 3):

FIGURE 2.
Mean Change in Total Symptom Score from Baseline Long-Term, Open-Label, Non-Placebo Controlled Study (N=494)

*p ≤ 0.05 vs. baseline mean baseline = 10.7

FIGURE 3.
Mean Change in Peak Flow Rate from Baseline Long-Term, Open-Label, Non-Placebo Controlled Study (N=494)

*p ≤ 0.05 vs. baseline; mean baseline = 9.9

In this long-term trial, both symptom scores and peak urinary flow rates showed statistically significant improvement suggesting a relaxation of smooth muscle cells.

Although blockade of alpha-1 adrenoceptors also lowers blood pressure in hypertensive patients with increased peripheral vascular resistance, terazosin treatment of normotensive men with BPH did not result in a clinically significant blood pressure lowering effect:

Mean Changes in Blood Pressure from Baseline to Final Visit in all Double-Blind, Placebo-Controlled Studies
 | Group | Normotensive Patients DBP ≤ 90 mm Hg |  | Hypertensive Patients DBP > 90 mm Hg
 | Group | N | Mean Change | N | Mean Change
SBP(mm Hg) | Placebo Terazosin | 293 519 | -0.1 -3.3 [p ≤ 0.05 vs. placebo] | 45 65 | -5.8 -14.4
DBP(mm Hg) | Placebo Terazosin | 293 519 | +0.4 -2.2 | 45 65 | -7.1 -15.1

B. Hypertension

In animals, terazosin causes a decrease in blood pressure by decreasing total peripheral vascular resistance. The vasodilatory hypotensive action of terazosin appears to be produced mainly by blockade of alpha-1 adrenoceptors. Terazosin decreases blood pressure gradually within 15 minutes following oral administration.

Patients in clinical trials of terazosin were administered once daily (the great majority) and twice daily regimens with total doses usually in the range of 5 to 20 mg/day, and had mild (about 77%, diastolic pressure 95 to 105 mmHg) or moderate (23%, diastolic pressure 105 to 115 mmHg) hypertension. Because terazosin, like all alpha antagonists, can cause unusually large falls in blood pressure after the first dose or first few doses, the initial dose was 1 mg in virtually all trials, with subsequent titration to a specified fixed dose or titration to some specified blood pressure end point (usually a supine diastolic pressure of 90 mmHg).

Blood pressure responses were measured at the end of the dosing interval (usually 24 hours) and effects were shown to persist throughout the interval, with the usual supine responses 5 to 10 mmHg systolic and 3.5 to 8 mmHg diastolic greater than placebo. The responses in the standing position tended to be somewhat larger, by 1 to 3 mmHg, although this was not true in all studies. The magnitude of the blood pressure responses was similar to prazosin and less than hydrochlorothiazide (in a single study of hypertensive patients). In measurements 24 hours after dosing, heart rate was unchanged.

Limited measurements of peak response (2 to 3 hours after dosing) during chronic terazosin administration indicate that it is greater than about twice the trough (24 hour) response, suggesting some attenuation of response at 24 hours, presumably due to a fall in blood terazosin concentrations at the end of the dose interval. This explanation is not established with certainty, however, and is not consistent with the similarity of blood pressure response to once daily and twice daily dosing and with the absence of an observed dose-response relationship over a range of 5 to 20 mg, i.e., if blood concentrations had fallen to the point of providing less than full effect at 24 hours, a shorter dosing interval or larger dose should have led to increased response.

Further dose response and dose duration studies are being carried out. Blood pressure should be measured at the end of the dose interval; if response is not satisfactory, patients may be tried on a larger dose or twice daily dosing regimen. The latter should also be considered if possibly blood pressure-related side effects, such as dizziness, palpitations, or orthostatic complaints, are seen within a few hours after dosing.

The greater blood pressure effect associated with peak plasma concentrations (first few hours after dosing) appears somewhat more position-dependent (greater in the erect position) than the effect of terazosin at 24 hours and in the erect position there is also a 6 to 10 beat per minute increase in heart rate in the first few hours after dosing. During the first 3 hours after dosing 12.5% of patients had a systolic pressure fall of 30 mmHg or more from supine to standing, or standing systolic pressure below 90 mmHg with a fall of at least 20 mmHg, compared to 4% of a placebo group.

There was a tendency for patients to gain weight during terazosin therapy. In placebo-controlled monotherapy trials, male and female patients receiving terazosin gained a mean of 1.7 and 2.2 pounds respectively, compared to losses of 0.2 and 1.2 pounds respectively in the placebo group. Both differences were statistically significant.

During controlled clinical trials, patients receiving terazosin monotherapy had a small but statistically significant decrease (a 3% fall) compared to placebo in total cholesterol and the combined low-density and very-low-density lipoprotein fractions. No significant changes were observed in high-density lipoprotein fraction and triglycerides compared to placebo.

Analysis of clinical laboratory data following administration of terazosin suggested the possibility of hemodilution based on decreases in hematocrit, hemoglobin, white blood cells, total protein and albumin. Decreases in hematocrit and total protein have been observed with alpha-blockade and are attributed to hemodilution.

Pharmacokinetics

Terazosin hydrochloride administered as capsules is essentially completely absorbed in man. Administration of capsules immediately after meals had a minimal effect on the extent of absorption. The time to reach peak plasma concentration however, was delayed by about 40 minutes. Terazosin has been shown to undergo minimal hepatic first-pass metabolism and nearly all of the circulating dose is in the form of parent drug. The plasma levels peak about one hour after dosing, and then decline with a half-life of approximately 12 hours. In a study that evaluated the effect of age on terazosin pharmacokinetics, the mean plasma half-lives were 14.0 and 11.4 hours for the age group ≥ 70 years and the age group of 20 to 39 years, respectively. After oral administration the plasma clearance was decreased by 31.7% in patients 70 years of age or older compared to that in patients 20 to 39 years of age.

The drug is 90 to 94% bound to plasma proteins and binding is constant over the clinically observed concentration range. Approximately 10% of an orally administered dose is excreted as parent drug in the urine and approximately 20% is excreted in the feces. The remainder is eliminated as metabolites. Impaired renal function had no significant effect on the elimination of terazosin, and dosage adjustment of terazosin to compensate for the drug removal during hemodialysis (approximately 10%) does not appear to be necessary. Overall, approximately 40% of the administered dose is excreted in the urine and approximately 60% in the feces. The disposition of the compound in animals is qualitatively similar to that in man.

INDICATIONS AND USAGE

Terazosin capsules are indicated for the treatment of symptomatic benign prostatic hyperplasia (BPH). There is a rapid response, with approximately 70% of patients experiencing an increase in urinary flow and improvement in symptoms of BPH when treated with terazosin capsules. The long-term effects of terazosin capsules on the incidence of surgery, acute urinary obstruction or other complications of BPH are yet to be determined.

Terazosin capsules are also indicated for the treatment of hypertension. Terazosin capsules can be used alone or in combination with other antihypertensive agents such as diuretics or beta-adrenergic blocking agents.

CONTRAINDICATIONS

Terazosin capsules are contraindicated in patients known to be hypersensitive to terazosin hydrochloride.

WARNINGS

Syncope and “First-dose” Effect

Terazosin capsules, like other alpha-adrenergic blocking agents, can cause marked lowering of blood pressure, especially postural hypotension, and syncope in association with the first dose or first few days of therapy. A similar effect can be anticipated if therapy is interrupted for several days and then restarted. Syncope has also been reported with other alpha-adrenergic blocking agents in association with rapid dosage increases or the introduction of another antihypertensive drug. Syncope is believed to be due to an excessive postural hypotensive effect, although occasionally the syncopal episode has been preceded by a bout of severe supraventricular tachycardia with heart rates of 120 to 160 beats per minute. Additionally, the possibility of the contribution of hemodilution to the symptoms of postural hypotension should be considered.

To decrease the likelihood of syncope or excessive hypotension, treatment should always be initiated with a 1 mg dose of terazosin capsules, given at bedtime. The 2 mg, 5 mg and 10 mg capsules are not indicated as initial therapy. Dosage should then be increased slowly, according to recommendations in the Dosage and Administration section and additional antihypertensive agents should be added with caution. The patient should be cautioned to avoid situations, such as driving or hazardous tasks, where injury could result should syncope occur during initiation of therapy.

In early investigational studies, where increasing single doses up to 7.5 mg were given at 3 day intervals, tolerance to the first dose phenomenon did not necessarily develop and the “first-dose” effect could be observed at all doses. Syncopal episodes occurred in 3 of the 14 subjects given terazosin at doses of 2.5, 5 and 7.5 mg, which are higher than the recommended initial dose; in addition, severe orthostatic hypotension (blood pressure falling to 50/0 mmHg) was seen in two others and dizziness, tachycardia, and lightheadedness occurred in most subjects. These adverse effects all occurred within 90 minutes of dosing.

In three placebo-controlled BPH studies 1, 2, and 3 (see CLINICAL PHARMACOLOGY), the incidence of postural hypotension in the terazosin treated patients was 5.1%, 5.2%, and 3.7% respectively.

In multiple dose clinical trials involving nearly 2000 hypertensive patients treated with terazosin capsules, syncope was reported in about 1% of patients. Syncope was not necessarily associated only with the first dose.

If syncope occurs, the patient should be placed in a recumbent position and treated supportively as necessary. There is evidence that the orthostatic effect of terazosin is greater, even in chronic use, shortly after dosing. The risk of the events is greatest during the initial seven days of treatment, but continues at all time intervals.

Priapism

Rarely, (probably less than once in every several thousand patients), terazosin and other α1-antagonists have been associated with priapism (painful penile erection, sustained for hours and unrelieved by sexual intercourse or masturbation). Two or three dozen cases have been reported. Because this condition can lead to permanent impotence if not promptly treated, patients must be advised about the seriousness of the condition (see PRECAUTIONS: Information for Patients).

PRECAUTIONS

General

Prostatic Cancer

Carcinoma of the prostate and BPH cause many of the same symptoms. These two diseases frequently co-exist. Therefore, patients thought to have BPH should be examined prior to starting terazosin capsule therapy to rule out the presence of carcinoma of the prostate.

Intraoperative Floppy Iris Syndrome (IFIS) has been observed during cataract surgery in some patients on/or previously treated with alpha-1 blockers. This variant of small pupil syndrome is characterized by the combination of a flaccid iris that billows in response to intraoperative irrigation currents, progressive intraoperative miosis despite preoperative dilation with standard mydriatic drugs, and potential prolapse of the iris toward the phacoemulsification incisions. The patient’s ophthalmologist should be prepared for possible modifications to their surgical technique, such as the utilization of iris hooks, iris dilator rings, or viscoelastic substances. There does not appear to be a benefit of stopping alpha-1 blocker therapy prior to cataract surgery.

Orthostatic Hypotension

While syncope is the most severe orthostatic effect of terazosin (see WARNINGS), other symptoms of lowered blood pressure, such as dizziness, lightheadedness and palpitations, were more common and occurred in some 28% of patients in clinical trials of hypertension. In BPH clinical trials, 21% of the patients experienced one or more of the following: dizziness, hypotension, postural hypotension, syncope, and vertigo. Patients with occupations in which such events represent potential problems should be treated with particular caution.

Information for Patients (see Patient Package Insert)

Patients should be made aware of the possibility of syncopal and orthostatic symptoms, especially at the initiation of therapy, and to avoid driving or hazardous tasks for 12 hours after the first dose, after a dosage increase, and after interruption of therapy when treatment is resumed. They should be cautioned to avoid situations where injury could result should syncope occur during initiation of terazosin therapy. They should also be advised of the need to sit or lie down when symptoms of lowered blood pressure occur, although these symptoms are not always orthostatic, and to be careful when rising from a sitting or lying position. If dizziness, lightheadedness, or palpitations are bothersome they should be reported to the physician, so that dose adjustment can be considered.

Patients should also be told that drowsiness or somnolence can occur with terazosin, requiring caution in people who must drive or operate heavy machinery.

Patients should be advised about the possibility of priapism as a result of treatment with terazosin capsules and other similar medications. Patients should know that this reaction to terazosin capsules is extremely rare, but that if it is not brought to immediate medical attention, it can lead to permanent erectile dysfunction (impotence).

Laboratory Tests

Small but statistically significant decreases in hematocrit, hemoglobin, white blood cells, total protein and albumin were observed in controlled clinical trials. These laboratory findings suggested the possibility of hemodilution. Treatment with terazosin capsules for up to 24 months had no significant effect on prostate specific antigen (PSA) levels.

Drug Interactions

In controlled trials, terazosin have been added to diuretics, and several beta-adrenergic blockers; no unexpected interactions were observed. Terazosin has also been used in patients on a variety of concomitant therapies; while these were not formal interaction studies, no interactions were observed. Terazosin has been used concomitantly in at least 50 patients on the following drugs or drug classes:

- analgesic/anti-inflammatory (e.g., acetaminophen, aspirin, codeine, ibuprofen, indomethacin);
- antibiotics (e.g., erythromycin, trimethoprim and sulfamethoxazole);
- anticholinergic/sympathomimetics (e.g., phenylephrine hydrochloride, phenylpropanolamine hydrochloride, pseudoephedrine hydrochloride);
- antigout (e.g., allopurinol);
- antihistamines (e.g., chlorpheniramine);
- cardiovascular agents (e.g., atenolol, hydrochlorothiazide, methyclothiazide, propranolol);
- corticosteroids;
- gastrointestinal agents (e.g., antacids);
- hypoglycemics;
- sedatives and tranquilizers (e.g., diazepam).

Use With Other Drugs

In a study (n=24) where terazosin and verapamil were administered concomitantly, terazosin’s mean AUC0-24 increased 11% after the first verapamil dose and after 3 weeks of verapamil treatment it increased by 24% with associated increases in Cmax (25%) and Cmin (32%) means. Terazosin mean Tmax decreased from 1.3 hours to 0.8 hours after 3 weeks of verapamil treatment. Statistically significant differences were not found in the verapamil level with and without terazosin. In a study (n=6) where terazosin and captopril were administered concomitantly, plasma disposition of captopril was not influenced by concomitant administration of terazosin and terazosin maximum plasma concentrations increased linearly with dose at steady-state after administration of terazosin plus captopril (see DOSAGE AND ADMINISTRATION).

Carcinogenesis, Mutagenesis, Impairment of Fertility :

Terazosin was devoid of mutagenic potential when evaluated in vivo and in vitro (the Ames test, in vivo cytogenetics, the dominant lethal test in mice, in vivo Chinese hamster chromosome aberration test and V79 forward mutation assay).

Terazosin administered in the feed to rats at doses of 8, 40, and 250 mg/kg/day (70, 350, and 2100 mg/M^2/day), for two years, was associated with a statistically significant increase in benign adrenal medullary tumors of male rats exposed to the 250 mg/kg dose. This dose is 175 times the maximum recommended human dose of 20 mg (12 mg/M^2). Female rats were unaffected. Terazosin was not oncogenic in mice when administered in feed for 2 years at a maximum tolerated dose of 32 mg/kg/day (110 mg/M^2; 9 times the maximum recommended human dose). The absence of mutagenicity in a battery of tests, of tumorigenicity of any cell type in the mouse carcinogenicity assay, of increased total tumor incidence in either species, and of proliferative adrenal lesions in female rats, suggests a male rat species-specific event. Numerous other diverse pharmaceutical and chemical compounds have also been associated with benign adrenal medullary tumors in male rats without supporting evidence for carcinogenicity in man.

The effect of terazosin on fertility was assessed in a standard fertility/reproductive performance study in which male and female rats were administered oral doses of 8, 30 and 120 mg/kg/day. Four of 20 male rats given 30 mg/kg (240 mg/M^2; 20 times the maximum recommended human dose) and five of 19 male rats given 120 mg/kg (960 mg/M^2; 80 times the maximum recommended human dose) failed to sire a litter. Testicular weights and morphology were unaffected by treatment. Vaginal smears at 30 and 120 mg/kg/day, however, appeared to contain less sperm than smears from control matings and good correlation was reported between sperm count and subsequent pregnancy.

Oral administration of terazosin for one or two years elicited a statistically significant increase in the incidence of testicular atrophy in rats exposed to 40 and 250 mg/kg/day (29 and 175 times the maximum recommended human dose), but not in rats exposed to 8 mg/kg/day (> 6 times the maximum recommended human dose). Testicular atrophy was also observed in dogs dosed with 300 mg/kg/day (> 500 times the maximum recommended human dose) for three months but not after one year when dosed with 20 mg/kg/day (38 times the maximum recommended human dose). This lesion has also been seen with Minipress®, another (marketed) selective-alpha-1 blocking agent.

Pregnancy

Teratogenic Effects :

Pregnancy Category C

Terazosin capsules were not teratogenic in either rats or rabbits when administered at oral doses up to 280 and 60 times, respectively, the maximum recommended human dose. Fetal resorptions occurred in rats dosed with 480 mg/kg/day, approximately 280 times the maximum recommended human dose. Increased fetal resorptions, decreased fetal weight and an increased number of supernumerary ribs were observed in offspring of rabbits dosed with 60 times the maximum recommended human dose. These findings (in both species) were most likely secondary to maternal toxicity. There are no adequate and well-controlled studies in pregnant women and the safety of terazosin in pregnancy has not been established. Terazosin capsules are not recommended during pregnancy unless the potential benefit justifies the potential risk to the mother and fetus.

Nonteratogenic Effects :

In a peri- and post-natal development study in rats, significantly more pups died in the group dosed with 120 mg/kg/day (> 75 times the maximum recommended human dose) than in the control group during the three-week postpartum period.

Nursing Mothers :

It is not known whether terazosin is excreted in breast milk. Because many drugs are excreted in breast milk, caution should be exercised when terazosin capsules are administered to a nursing woman.

Pediatric Use :

Safety and effectiveness in pediatric patients have not been determined.

ADVERSE REACTIONS

Benign Prostatic Hyperplasia

The incidence of treatment-emergent adverse events has been ascertained from clinical trials conducted worldwide. All adverse events reported during these trials were recorded as adverse reactions. The incidence rates presented below are based on combined data from six placebo-controlled trials involving once-a-day administration of terazosin at doses ranging from 1 to 20 mg. Table 1 summarizes those adverse events reported for patients in these trials when the incidence rate in the terazosin group was at least 1%, and was greater than that for the placebo group, or where the reaction is of clinical interest. Asthenia, postural hypotension, dizziness, somnolence, nasal congestion/rhinitis, and impotence were the only events that were significantly (p ≤ 0.05) more common in patients receiving terazosin than in patients receiving placebo. The incidence of urinary tract infection was significantly lower in the patients receiving terazosin than in patients receiving placebo. An analysis of the incidence rate of hypotensive adverse events (see PRECAUTIONS) adjusted for the length of drug treatment has shown that the risk of the events is greatest during the initial seven days of treatment, but continues at all time intervals.

TABLE 1. Adverse Reactions During Placebo-Controlled Trials Benign Prostatic Hyperplasia
Body System | Terazosin (N = 636) | Placebo (N = 360)
BODY AS A WHOLE [Includes weakness, tiredness, lassitude, and fatigue.] Asthenia Flu Syndrome Headache | 7.4% [p ≤ 0.05 comparison between groups.] 2.4% 4.9% | 3.3% 1.7% 5.8%
CARDIOVASCULAR SYSTEM Hypotension Palpitations Postural Hypotension Syncope | 0.6% 0.9% 3.9% 0.6% | 0.6% 1.1% 0.8% 0.0%
DIGESTIVE SYSTEM Nausea | 1.7% | 1.1%
METABOLIC AND NUTRITIONAL DISORDERS Peripheral Edema Weight Gain | 0.9% 0.5% | 0.3% 0.0%
NERVOUS SYSTEM Dizziness Somnolence Vertigo | 9.1% 3.6% 1.4% | 4.2% 1.9% 0.3%
RESPIRATORY SYSTEM Dyspnea Nasal Congestion/Rhinitis | 1.7% 1.9% | 0.8% 0.0%
SPECIAL SENSES Blurred Vision/Amblyopia | 1.3% | 0.6%
UROGENITAL SYSTEM Impotence Urinary Tract Infection | 1.6% 1.3% | 0.6% 3.9%

Additional adverse events have been reported, but these are, in general, not distinguishable from symptoms that might have occurred in the absence of exposure to terazosin. The safety profile of patients treated in the long-term open-label study was similar to that observed in the controlled studies.

The adverse events were usually transient and mild or moderate in intensity, but sometimes were serious enough to interrupt treatment. In the placebo-controlled clinical trials, the rates of premature termination due to adverse events were not statistically different between the placebo and terazosin groups. The adverse events that were bothersome, as judged by their being reported as reasons for discontinuation of therapy by at least 0.5% of the terazosin group and being reported more often than in the placebo group, are shown in Table 2.

TABLE 2. Discontinuation During Placebo-Controlled Trials Benign Prostatic Hyperplasia
Body System | Terazosin (N = 636) | Placebo (N = 360)
BODY AS A WHOLE Fever Headache | 0.5% 1.1% | 0.0% 0.8%
CARDIOVASCULAR SYSTEM Postural Hypotension Syncope | 0.5% 0.5% | 0.0% 0.0%
DIGESTIVE SYSTEM Nausea | 0.5% | 0.3%
NERVOUS SYSTEM Dizziness Vertigo | 2.0% 0.5% | 1.1% 0.0%
RESPIRATORY SYSTEM Dyspnea | 0.5% | 0.3%
SPECIAL SENSES Blurred Vision/Amblyopia | 0.6% | 0.0%
UROGENITAL SYSTEM Urinary Tract Infection | 0.5% | 0.3%

Hypertension

The prevalence of adverse reactions has been ascertained from clinical trials conducted primarily in the United States. All adverse experiences (events) reported during these trials were recorded as adverse reactions. The prevalence rates presented below are based on combined data from fourteen placebo-controlled trials involving once-a-day administration of terazosin, as monotherapy or in combination with other antihypertensive agents, at doses ranging from 1 to 40 mg. Table 3 summarizes those adverse experiences reported for patients in these trials where the prevalence rate in the terazosin group was at least 5%, where the prevalence rate for the terazosin group was at least 2% and was greater than the prevalence rate for the placebo group, or where the reaction is of particular interest. Asthenia, blurred vision, dizziness, nasal congestion, nausea, peripheral edema, palpitations and somnolence were the only symptoms that were significantly (p < 0.05) more common in patients receiving terazosin than in patients receiving placebo. Similar adverse reaction rates were observed in placebo-controlled monotherapy trials.

TABLE 3. Adverse Reactions During Placebo-Controlled Trials Hypertension
Body System | Terazosin (N = 859) | Placebo (N = 506)
BODY AS A WHOLE [Includes weakness, tiredness, lassitude, and fatigue.] Asthenia Back Pain Headache | 11.3% [Statistically significant at p=0.05 level.] 2.4% 16.2% | 4.3% 1.2% 15.8%
CARDIOVASCULAR SYSTEM Palpitations Postural Hypotension Tachycardia | 4.3% 1.3% 1.9% | 1.2% 0.4% 1.2%
DIGESTIVE SYSTEM Nausea | 4.4% | 1.4%
METABOLIC AND NUTRITIONAL DISORDERS Edema Peripheral Edema Weight Gain | 0.9% 5.5% 0.5% | 0.6% 2.4% 0.2%
MUSCULOSKELETAL SYSTEM Pain – Extremities | 3.5% | 3.0%
NERVOUS SYSTEM Depression Dizziness Libido Decreased Nervousness Paresthesia Somnolence | 0.3% 19.3% 0.6% 2.3% 2.9% 5.4% | 0.2% 7.5% 0.2% 1.8% 1.4% 2.6%
RESPIRATORY SYSTEM Dyspnea Nasal Congestion Sinusitis | 3.1% 5.9% 2.6% | 2.4% 3.4% 1.4%
SPECIAL SENSES Blurred Vision | 1.6% | 0.0%
UROGENITAL SYSTEM Impotence | 1.2% | 1.4%

Additional adverse reactions have been reported, but these are, in general, not distinguishable from symptoms that might have occurred in the absence of exposure to terazosin. The following additional adverse reactions were reported by at least 1% of 1987 patients who received terazosin in controlled or open, short- or long-term clinical trials or have been reported during marketing experience:

Body as a Whole :

Chest pain, facial edema, fever, abdominal pain, neck pain, shoulder pain.

Cardiovascular System :

Arrhythmia, vasodilation.

Digestive System :

Constipation, diarrhea, dry mouth, dyspepsia, flatulence, vomiting.

Metabolic/Nutritional Disorders

Gout.

Musculoskeletal System :

Arthralgia, arthritis, joint disorder, myalgia.

Nervous System :

Anxiety, insomnia.

Respiratory System :

Bronchitis, cold symptoms, epistaxis, flu symptoms, increased cough, pharyngitis, rhinitis.

Skin and Appendages :

Pruritus, rash, sweating.

Special Senses :

Abnormal vision, conjunctivitis, tinnitus.

Urogenital System :

Urinary frequency, urinary incontinence primarily reported in postmenopausal women, urinary tract infection.

The adverse reactions were usually mild or moderate in intensity but sometimes were serious enough to interrupt treatment. The adverse reactions that were most bothersome, as judged by their being reported as reasons for discontinuation of therapy by at least 0.5% of the terazosin group and being reported more often than in the placebo group, are shown in Table 4.

TABLE 4. Discontinuations During Placebo-Controlled Trials Hypertension
Body System | Terazosin (N = 859) | Placebo (N = 506)
BODY AS A WHOLE Asthenia Headache | 1.6% 1.3% | 0.0% 1.0%
CARDIOVASCULAR SYSTEM Palpitations Postural Hypotension Syncope Tachycardia | 1.4% 0.5% 0.5% 0.6% | 0.2% 0.0% 0.2% 0.0%
DIGESTIVE SYSTEM Nausea | 0.8% | 0.0%
METABOLIC AND NUTRITIONAL DISORDERS Peripheral Edema | 0.6% | 0.0%
NERVOUS SYSTEM Dizziness Paresthesia Somnolence | 3.1% 0.8% 0.6% | 0.4% 0.2% 0.2%
RESPIRATORY SYSTEM Dyspnea Nasal Congestion | 0.9% 0.6% | 0.6% 0.0%
SPECIAL SENSES Blurred Vision | 0.6% | 0.0%

Post-marketing experience indicates that in rare instances patients may develop allergic reactions, including anaphylaxis, following administration of terazosin hydrochloride. There have been reports of priapism and thrombocytopenia during post-marketing surveillance. Atrial fibrillation has been reported.

During cataract surgery, a variant of small pupil syndrome known as Intraoperative Floppy Iris Syndrome (IFIS) has been reported in association with alpha-1 blocker therapy (see PRECAUTIONS).

OVERDOSAGE

Should overdosage of terazosin capsules lead to hypotension, support of the cardiovascular system is of first importance. Restoration of blood pressure and normalization of heart rate may be accomplished by keeping the patient in the supine position. If this measure is inadequate, shock should first be treated with volume expanders. If necessary, vasopressors should then be used and renal function should be monitored and supported as needed. Laboratory data indicate that terazosin is 90-94% protein bound; therefore, dialysis may not be of benefit.

DOSAGE AND ADMINISTRATION

If terazosin capsules administration is discontinued for several days, therapy should be reinstituted using the initial dosing regimen.

Benign Prostatic Hyperplasia

Initial Dose :

1 mg at bedtime is the starting dose for all patients, and this dose should not be exceeded as an initial dose. Patients should be closely followed during initial administration in order to minimize the risk of severe hypotensive response.

Subsequent Doses :

The dose should be increased in a stepwise fashion to 2 mg, 5 mg, or 10 mg once daily to achieve the desired improvement of symptoms and/or flow rates. Doses of 10 mg once daily are generally required for the clinical response. Therefore, treatment with 10 mg for a minimum of 4 to 6 weeks may be required to assess whether a beneficial response has been achieved. Some patients may not achieve a clinical response despite appropriate titration. Although some additional patients responded at a 20 mg daily dose, there was an insufficient number of patients studied to draw definitive conclusions about this dose. There are insufficient data to support the use of higher doses for those patients who show inadequate or no response to 20 mg daily. If terazosin administration is discontinued for several days or longer, therapy should be reinstituted using the initial dosing regimen.

Use With Other Drugs :

Caution should be observed when terazosin capsules are administered concomitantly with other antihypertensive agents, especially the calcium channel blocker verapamil, to avoid the possibility of developing significant hypotension. When using terazosin capsules and other antihypertensive agents concomitantly, dosage reduction and retitration of either agent may be necessary (see PRECAUTIONS).
Hypotension has been reported when terazosin capsules have been used with phosphodiesterase-5 (PDE-5) inhibitors.

Hypertension

The dose of terazosin capsules and the dose interval (12 or 24 hours) should be adjusted according to the patient’s individual blood pressure response. The following is a guide to its administration:

Initial Dose

1 mg at bedtime is the starting dose for all patients, and this dose should not be exceeded. This initial dosing regimen should be strictly observed to minimize the potential for severe hypotensive effects.

Subsequent Doses

The dose may be slowly increased to achieve the desired blood pressure response. The usual recommended dose range is 1 mg to 5 mg administered once a day; however, some patients may benefit from doses as high as 20 mg per day. Doses over 20 mg do not appear to provide further blood pressure effect and doses over 40 mg have not been studied. Blood pressure should be monitored at the end of the dosing interval to be sure control is maintained throughout the interval. It may also be helpful to measure blood pressure 2 to 3 hours after dosing to see if the maximum and minimum responses are similar, and to evaluate symptoms such as dizziness or palpitations which can result from excessive hypotensive response. If response is substantially diminished at 24 hours an increased dose or use of a twice daily regimen can be considered. If terazosin administration is discontinued for several days or longer, therapy should be reinstituted using the initial dosing regimen. In clinical trials, except for the initial dose, the dose was given in the morning.

Use With Other Drugs

(See above.)

PATIENT INFORMATION ABOUT

TERAZOSIN CAPSULES, USP
Rx Only
Generic Name: Terazosin (Ter-A-so-sin)

When used to treat HYPERTENSION or BENIGN PROSTATIC HYPERPLASIA (BPH)

Please read this leaflet before you start taking terazosin capsules. Also, read it each time you get a new prescription. This is a summary and should NOT take the place of a full discussion with your doctor who has additional information about Terazosin Capsules. You and your doctor should discuss Terazosin Capsules and your condition before you start taking it and at your regular checkups.

Terazosin Capsules are used to treat high blood pressure (hypertension). Terazosin Capsules are also used to treat benign prostatic hyperplasia (BPH) in men. This leaflet describes Terazosin Capsules as a treatment for hypertension or BPH.

What is hypertension (high blood pressure)?

Blood pressure is the tension of the blood within the blood vessels. If blood is pumped too forcefully, or if the blood vessels are too narrow, the pressure of the blood against the walls of the vessels rises.

If high blood pressure is not treated, over time, the increased pressure can damage blood vessels or it can cause the heart to work too hard and may decrease the flow of blood to the heart, brain, and kidneys. As a result, these organs may become damaged and not function correctly. If high blood pressure is controlled, this damage is less likely to happen.

Treatment options for hypertension

Non-drug treatments are sometimes effective in controlling mild hypertension. The most important lifestyle changes to lower blood pressure are to lose weight, reduce salt, fat, and alcohol in the diet, quit smoking, and exercise regularly. However, many hypertensive patients require one or more ongoing medications to control their blood pressure. There are different kinds of medications used to treat hypertension. Your doctor has prescribed Terazosin Capsules for you.

What Terazosin Capsules do to treat hypertension

Terazosin capsules work by relaxing blood vessels so that blood passes through them more easily. This helps to lower blood pressure.

What is BPH?

The prostate is a gland located below the bladder of men. It surrounds the urethra (you-REETH-rah), which is a tube that drains urine from the bladder. BPH is an enlargement of the prostate gland. The symptoms of BPH, however, can be caused by an increase in the tightness of muscles in the prostate. If the muscles inside the prostate tighten, they can squeeze the urethra and slow the flow of urine. This can lead to symptoms such as:

- a weak or interrupted stream when urinating
- a feeling that you cannot empty your bladder completely
- a feeling of delay when you start to urinate
- a need to urinate often, especially at night, or
- a feeling that you must urinate right away.

Treatment options for BPH

There are three main treatment options for BPH:

- Program of monitoring or “Watchful Waiting”. Some men have an enlarged prostate gland, but no symptoms, or symptoms that are not bothersome. If this applies, you and your doctor may decide on a program of monitoring including regular checkups, instead of medication or surgery.
- Medication. There are different kinds of medication used to treat BPH. Your doctor has prescribed Terazosin Capsules for you. See “What Terazosin Capsules do to treat BPH” below.
- Surgery. Some patients may need surgery. Your doctor can describe several different surgical procedures to treat BPH. Which procedure is best depends on your symptoms and medical condition.

What Terazosin Capsules do to treat BPH

Terazosin Capsules relax the tightness of a certain type of muscle in the prostate and at the opening of the bladder. This may increase the rate of urine flow and/or decrease the symptoms you are having.

- Terazosin Capsules help relieve the symptoms of BPH. It does NOT change the size of the prostate, which may continue to grow. However, a larger prostate does not necessarily cause more or worse symptoms.
- If Terazosin Capsules are helping you, you should notice an effect on your particular symptoms in 2 to 4 weeks of starting to take the medication.
- Even though you take Terazosin Capsules and they may help you, Terazosin Capsules may not prevent the need for surgery in the future.

Other important facts about Terazosin Capsules for BPH

- You should see an effect on your symptoms in 2 to 4 weeks. So, you will need to continue seeing your doctor to check your progress regarding your BPH and to monitor your blood pressure in addition to your other regular checkups.
- Your doctor has prescribed Terazosin Capsules for your BPH and not for prostate cancer. However, a man can have BPH and prostate cancer at the same time. Doctors usually recommend that men be checked for prostate cancer once a year when they turn 50 (or 40 if a family member has had prostate cancer). These checks should continue even if you are taking Terazosin Capsules. Terazosin Capsules are not a treatment for prostate cancer.
- About Prostate Specific Antigen (PSA). Your doctor may have done a blood test called PSA. Your doctor is aware that Terazosin Capsules do not affect PSA levels. You may want to ask your doctor more about this if you have had a PSA test done.

What you should know while taking Terazosin Capsules for hypertension or BPH

WARNINGS

Terazosin Capsules Can Cause a Sudden Drop in Blood Pressure After the VERY FIRST DOSE. You may feel dizzy, faint, or “light-headed” particularly after you get up from bed or from a chair. This is more likely to occur after you’ve taken the first few doses, but can occur at any time while you are taking the drug. It can also occur if you stop taking the drug and then re-start treatment.

Because of this effect, your doctor may have told you to take Terazosin Capsules at bedtime. If you take Terazosin Capsules at bedtime but need to get up from bed to go to the bathroom, get up slowly and cautiously until you are sure how the medicine affects you. It is also important to get up slowly from a chair or bed at any time until you learn how you react to Terazosin Capsules. You should not drive or do any hazardous tasks until you are used to the effects of the medication. If you begin to feel dizzy, sit or lie down until you feel better.

- You will start with a 1 mg dose of Terazosin Capsules. Then the dose will be increased as your body gets used to the effect of the medication.
- Other side effects you could have while taking Terazosin Capsules include drowsiness, blurred or hazy vision, nausea, or “puffiness” of the feet or hands. Discuss any unexpected effects you notice with your doctor.

Extremely rarely, Terazosin Capsules and similar medications have caused painful erection of the penis, sustained for hours and unrelieved by sexual intercourse or masturbation. This condition is serious, and if untreated it can be followed by permanent inability to have an erection. If you have a prolonged abnormal erection, call your doctor or go to an emergency room as soon as possible.

How to take Terazosin Capsules

Follow your doctor’s instructions about how to take Terazosin Capsules. You must take it every day at the dose prescribed. Talk with your doctor if you don’t take it for a few days, you may have to restart it at a 1 mg dose and be cautious about possible dizziness. Do not share Terazosin Capsules with anyone else; it was prescribed only for you.

Keep Terazosin Capsules and all medicines out of the reach of children.

Store at 20°-25°C (68°-77°F) (see USP Controlled Room Temperature).

Protect from light and moisture.

FOR MORE INFORMATION ABOUT TERAZOSIN CAPSULES AND HYPERTENSION OR BPH, TALK WITH YOUR DOCTOR, NURSE, PHARMACIST OR OTHER HEALTH CARE PROVIDER.

Revised 07/25
Jubilant Cadista Pharmaceuticals Inc.
For additional copies of the printed patient information leaflet/medication guide, please visit www.cadista.com or call 1-800-313-4623.

HOW SUPPLIED

Product: 50090-1559

NDC: 50090-1559-0 30 CAPSULE in a BOTTLE

NDC: 50090-1559-1 90 CAPSULE in a BOTTLE

Product: 50090-2371

NDC: 50090-2371-0 30 CAPSULE in a BOTTLE

Product: 50090-2623

NDC: 50090-2623-0 30 CAPSULE in a BOTTLE

NDC: 50090-2623-1 90 CAPSULE in a BOTTLE